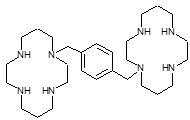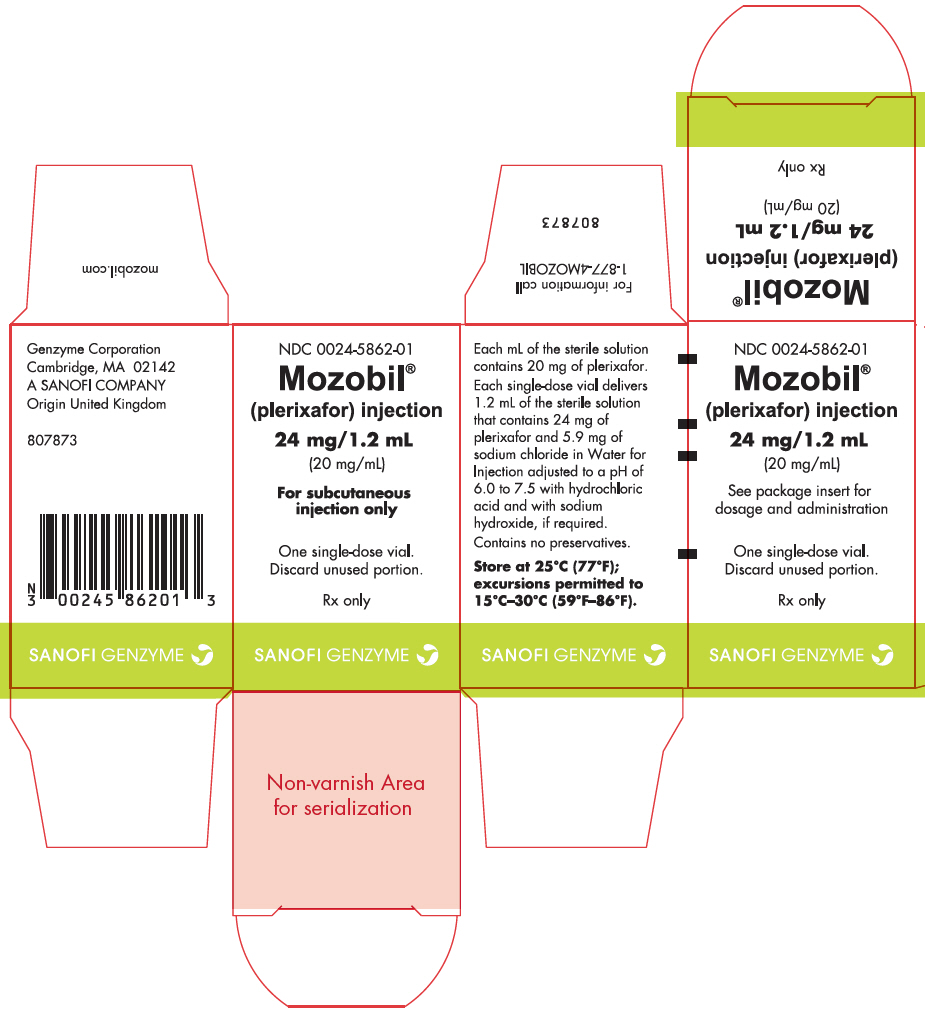 DRUG LABEL: Mozobil
NDC: 0024-5862 | Form: INJECTION, SOLUTION
Manufacturer: Sanofi-Aventis U.S. LLC
Category: prescription | Type: HUMAN PRESCRIPTION DRUG LABEL
Date: 20250922

ACTIVE INGREDIENTS: PLERIXAFOR 24 mg/1.2 mL
INACTIVE INGREDIENTS: SODIUM CHLORIDE 5.9 mg/1.2 mL; HYDROCHLORIC ACID; WATER; SODIUM HYDROXIDE

HIGHLIGHTS OF PRESCRIBING INFORMATION

These highlights do not include all the information needed to use MOZOBIL safely and effectively. See full prescribing information for MOZOBIL.
MOZOBIL® (plerixafor) injection, for subcutaneous use
Initial U.S. Approval: 2008

1 INDICATIONS AND USAGE

Mozobil, a hematopoietic stem cell mobilizer, is indicated in combination with filgrastim to mobilize hematopoietic stem cells (HSCs) to the peripheral blood for collection and subsequent autologous transplantation in patients with non-Hodgkin's lymphoma or multiple myeloma. (1)

2 DOSAGE AND ADMINISTRATION

- Initiate Mozobil treatment after the patient has received filgrastim once daily for 4 days. (2.1)
- Repeat Mozobil dose up to 4 consecutive days. (2.1)
- Dose based on patient weight
  - Less than or equal to 83 kg: 20 mg dose or select dose based on 0.24 mg/kg actual body weight. (2.1)
  - greater than 83 kg: select dose based on 0.24 mg/kg actual body weight. (2.1)
- Administer by subcutaneous injection approximately 11 hours prior to initiation of apheresis. (2.1)
- Renal impairment: If creatinine clearance is ≤50 mL/min, decrease dose by one-third to 0.16 mg/kg. (2.3)

3 DOSAGE FORMS AND STRENGTHS

- Injection: 24 mg/1.2 mL (20 mg/mL) in a single-dose vial. (3)

4 CONTRAINDICATIONS

- History of hypersensitivity to Mozobil. (4)

5 WARNINGS AND PRECAUTIONS

- Anaphylactic Shock and Serious Hypersensitivity Reactions have occurred. Monitor patients during and after completion of Mozobil administration. (5.1)
- Tumor Cell Mobilization in Leukemia Patients: Mozobil may mobilize leukemic cells and should not be used in leukemia patients. (5.2)
- Hematologic Effects: Increased circulating leukocytes and decreased platelet counts have been observed. Monitor blood cell counts and platelet counts during Mozobil use. (5.3)
- Potential for Tumor Cell Mobilization: Tumor cells may be released from marrow during HSC mobilization with Mozobil and filgrastim. Effect of reinfusion of tumor cells is unknown. (5.4)
- Splenic Rupture: Evaluate patients who report left upper abdominal and/or scapular or shoulder pain. (5.5)
- Embryo-Fetal Toxicity: Can cause fetal harm. Advise women not to become pregnant when taking Mozobil. (5.6, 8.1)

6 ADVERSE REACTIONS

Most common adverse reactions (≥10%): diarrhea, nausea, fatigue, injection site reactions, headache, arthralgia, dizziness, and vomiting. (6)

To report SUSPECTED ADVERSE REACTIONS, contact Genzyme Corporation at 1-877-4MOZOBIL or FDA at 1-800-FDA-1088 or www.fda.gov/medwatch.

8 USE IN SPECIFIC POPULATIONS

Lactation: Advise not to breastfeed. (8.2)

FULL PRESCRIBING INFORMATION

1 INDICATIONS AND USAGE

Mozobil is indicated in combination with filgrastim to mobilize hematopoietic stem cells (HSCs) to the peripheral blood for collection and subsequent autologous transplantation in patients with non-Hodgkin's lymphoma (NHL) or multiple myeloma (MM).

2 DOSAGE AND ADMINISTRATION

2.1 Recommended Dosage and Administration

Begin treatment with Mozobil after the patient has received filgrastim once daily for 4 days [see Dosage and Administration (2.2)]. Administer Mozobil approximately 11 hours prior to initiation of each apheresis for up to 4 consecutive days.

The recommended dose of Mozobil by subcutaneous injection is based on body weight:

- 20 mg fixed dose or 0.24 mg/kg of body weight for patients weighing less than or equal to 83 kg. [see Clinical Pharmacology (12.3)]
- 0.24 mg/kg of body weight for patients weighing greater than 83 kg

Use the patient's actual body weight to calculate the volume of Mozobil to be administered. Each vial delivers 1.2 mL of 20 mg/mL solution, and the volume to be administered to patients should be calculated from the following equation:

0.012 × patient's actual body weight (in kg) = volume to be administered (in mL)

In clinical studies, Mozobil dose has been calculated based on actual body weight in patients up to 175% of ideal body weight. Mozobil dose and treatment of patients weighing more than 175% of ideal body weight have not been investigated.

Based on increasing exposure with increasing body weight, the Mozobil dose should not exceed 40 mg/day [see Clinical Pharmacology (12.3)].

Vials should be inspected visually for particulate matter and discoloration prior to administration and should not be used if there is particulate matter or if the solution is discolored.

Discard unused portion.

2.2 Recommended Concomitant Medications

Administer daily morning doses of filgrastim 10 mcg/kg for 4 days prior to the first evening dose of Mozobil and on each day prior to apheresis [see Clinical Studies (14)].

2.3 Dose Modifications in Renal Impairment

In patients with moderate and severe renal impairment (estimated creatinine clearance (CLCR) less than or equal to 50 mL/min), reduce the dose of Mozobil by one-third based on body weight category as shown in Table 1. If CLCR is less than or equal to 50 mL/min the dose should not exceed 27 mg/day, as the mg/kg-based dosage results in increased plerixafor exposure with increasing body weight [see Clinical Pharmacology (12.3)]. Similar systemic exposure is predicted if the dose is reduced by one-third in patients with moderate and severe renal impairment compared with subjects with normal renal function [see Clinical Pharmacology (12.3)].

Table 1: Recommended Dosage of Mozobil in Patients with Renal Impairment
Estimated Creatinine Clearance (mL/min) | Dose
 | Body Weight less than or equal to 83 kg | Body Weight greater than 83 kg and less than 160 kg
greater than 50 | 20 mg or 0.24 mg/kg once daily | 0.24 mg/kg once daily (not to exceed 40 mg/day)
less than or equal to 50 | 13 mg or 0.16 mg/kg once daily | 0.16 mg/kg once daily (not to exceed 27 mg/day)

The following (Cockcroft-Gault) formula may be used to estimate CLCR:

Males:
Creatinine clearance (mL/min) = weight (kg) × (140 – age in years)
72 × serum creatinine (mg/dL)

Females:
Creatinine clearance (mL/min) = 0.85 × value calculated for males

There is insufficient information to make dosage recommendations in patients on hemodialysis.

3 DOSAGE FORMS AND STRENGTHS

Injection: 24 mg/1.2 mL (20 mg/mL) sterile, clear, colorless to pale-yellow solution in a single-dose vial.

4 CONTRAINDICATIONS

Mozobil is contraindicated in patients with a history of hypersensitivity to plerixafor [see Warnings and Precautions (5.1)]. Anaphylactic shock has occurred with use of Mozobil.

5 WARNINGS AND PRECAUTIONS

5.1 Anaphylactic Shock and Hypersensitivity Reactions

Serious hypersensitivity reactions, including anaphylactic-type reactions, some of which have been life-threatening with clinically significant hypotension and shock have occurred in patients receiving Mozobil [see Adverse Reactions (6.2)]. Observe patients for signs and symptoms of hypersensitivity during and after Mozobil administration for at least 30 minutes and until clinically stable following completion of each administration. Only administer Mozobil when personnel and therapies are immediately available for the treatment of anaphylaxis and other hypersensitivity reactions.

In clinical studies, mild or moderate allergic reactions occurred within approximately 30 minutes after Mozobil administration in less than 1% of patients [see Adverse Reactions (6.1)].

5.2 Tumor Cell Mobilization in Leukemia Patients

For the purpose of HSC mobilization, Mozobil may cause mobilization of leukemic cells and subsequent contamination of the apheresis product. Therefore, Mozobil is not intended for HSC mobilization and harvest in patients with leukemia.

5.3 Hematologic Effects

Leukocytosis

Administration of Mozobil in conjunction with filgrastim increases circulating leukocytes as well as HSC populations. Monitor white blood cell counts during Mozobil use [see Adverse Reactions (6.1)].

Thrombocytopenia

Thrombocytopenia has been observed in patients receiving Mozobil. Monitor platelet counts in all patients who receive Mozobil and then undergo apheresis.

5.4 Potential for Tumor Cell Mobilization

When Mozobil is used in combination with filgrastim for HSC mobilization‚ tumor cells may be released from the marrow and subsequently collected in the leukapheresis product. The effect of potential reinfusion of tumor cells has not been well-studied.

5.5 Splenic Enlargement and Rupture

Higher absolute and relative spleen weights associated with extramedullary hematopoiesis were observed following prolonged (2 to 4 weeks) daily plerixafor SC administration in rats at doses approximately 4-fold higher than the recommended human dose based on body surface area. The effect of Mozobil on spleen size in patients was not specifically evaluated in clinical studies. Cases of splenic enlargement and/or rupture have been reported following the administration of Mozobil in conjunction with filgrastim. Evaluate individuals receiving Mozobil in combination with filgrastim who report left upper abdominal pain and/or scapular or shoulder pain for splenic integrity.

5.6 Embryo-Fetal Toxicity

Based on findings from animal reproduction studies, Mozobil can cause fetal harm when administered to a pregnant woman. Plerixafor administration to pregnant rats during organogenesis resulted in embryo-fetal mortality, structural abnormalities, and alterations to growth at exposures approximately 10 times the exposure at the recommended human dose.

Advise pregnant women of the potential risk to the fetus. Advise females of reproductive potential to use an effective form of contraception during treatment with Mozobil and for one week after the final dose [see Use in Specific Populations (8.1)].

6 ADVERSE REACTIONS

The following clinically significant adverse reactions are discussed elsewhere in the labeling:

- Anaphylactic shock and hypersensitivity reactions [see Warnings and Precautions (5.1)]
- Potential for tumor cell mobilization in leukemia patients [see Warnings and Precautions (5.2)]
- Increased circulating leukocytes and decreased platelet counts [see Warnings and Precautions (5.3)]
- Potential for tumor cell mobilization [see Warnings and Precautions (5.4)]
- Splenic enlargement [see Warnings and Precautions (5.5)]

6.1 Clinical Trials Experience

Because clinical trials are conducted under widely varying conditions, adverse reaction rates observed in the clinical trials of a drug cannot be directly compared to rates in the clinical trials of another drug and may not reflect the rates observed in practice.

The most common adverse reactions (≥10%) reported in patients who received Mozobil in conjunction with filgrastim regardless of causality and more frequent with Mozobil than placebo during HSC mobilization and apheresis were diarrhea, nausea, fatigue, injection site reactions, headache, arthralgia, dizziness, and vomiting.

Safety data for Mozobil in combination with filgrastim were obtained from two randomized placebo-controlled studies (301 patients) and 10 uncontrolled studies (242 patients). Patients were primarily treated with Mozobil at daily doses of 0.24 mg/kg SC. Median exposure to Mozobil in these studies was 2 days (range 1 to 7 days).

In the two randomized studies in patients with NHL and MM, a total of 301 patients were treated in the Mozobil and filgrastim group and 292 patients were treated in the placebo and filgrastim group. Patients received daily morning doses of filgrastim 10 mcg/kg for 4 days prior to the first dose of Mozobil 0.24 mg/kg SC or placebo and on each morning prior to apheresis. The adverse reactions that occurred in ≥5% of the patients who received Mozobil regardless of causality and were more frequent with Mozobil than placebo during HSC mobilization and apheresis are shown in Table 2.

Table 2: Adverse Reactions in ≥5% of Non-Hodgkin's Lymphoma and Multiple Myeloma Patients Receiving Mozobil and More Frequent than Placebo during HSC Mobilization and Apheresis
 | Percent of Patients (%)
 | Mozobil and Filgrastim (n=301) |  |  | Placebo and Filgrastim (n=292)
 | All Grades [Grades based on criteria from the World Health Organization (WHO)] | Grade 3 | Grade 4 | All Grades | Grade 3 | Grade 4
Gastrointestinal disorders
Diarrhea | 37 | <1 | 0 | 17 | 0 | 0
Nausea | 34 | 1 | 0 | 22 | 0 | 0
Vomiting | 10 | <1 | 0 | 6 | 0 | 0
Flatulence | 7 | 0 | 0 | 3 | 0 | 0
General disorders and administration site conditions
Injection site reactions | 34 | 0 | 0 | 10 | 0 | 0
Fatigue | 27 | 0 | 0 | 25 | 0 | 0
Musculoskeletal and connective tissue disorders
Arthralgia | 13 | 0 | 0 | 12 | 0 | 0
Nervous system disorders
Headache | 22 | <1 | 0 | 21 | 1 | 0
Dizziness | 11 | 0 | 0 | 6 | 0 | 0
Psychiatric disorders
Insomnia | 7 | 0 | 0 | 5 | 0 | 0

In the randomized studies, 34% of patients with NHL or MM had mild to moderate injection site reactions at the site of subcutaneous administration of Mozobil. These included erythema, hematoma, hemorrhage, induration, inflammation, irritation, pain, paresthesia, pruritus, rash, swelling, and urticaria.

Mild to moderate allergic reactions were observed in less than 1% of patients within approximately 30 min after Mozobil administration, including one or more of the following: urticaria (n=2), periorbital swelling (n=2), dyspnea (n=1) or hypoxia (n=1). Symptoms generally responded to treatments (e.g., antihistamines, corticosteroids, hydration or supplemental oxygen) or resolved spontaneously.

Vasovagal reactions, orthostatic hypotension, and/or syncope can occur following subcutaneous injections. In Mozobil oncology and healthy volunteer clinical studies, less than 1% of subjects experienced vasovagal reactions following subcutaneous administration of Mozobil doses ≤0.24 mg/kg. The majority of these events occurred within 1 hour of Mozobil administration. Because of the potential for these reactions, appropriate precautions should be taken.

Other adverse reactions in the randomized studies that occurred in <5% of patients but were reported as related to Mozobil during HSC mobilization and apheresis included abdominal pain, hyperhidrosis, abdominal distention, dry mouth, erythema, stomach discomfort, malaise, hypoesthesia oral, constipation, dyspepsia, and musculoskeletal pain.

Hyperleukocytosis: In clinical trials, white blood cell counts of 100,000/mcL or greater were observed, on the day prior to or any day of apheresis, in 7% of patients receiving Mozobil and in 1% of patients receiving placebo. No complications or clinical symptoms of leukostasis were observed.

6.2 Postmarketing Experience

In addition to adverse reactions reported from clinical trials, the following adverse reactions have been reported from postmarketing experience with Mozobil. Because these reactions are reported voluntarily from a population of uncertain size, it is not always possible to reliably estimate their frequency or establish a causal relationship to drug exposure.

Blood and Lymphatic System: Splenomegaly and splenic rupture

Immune System Disorders: Anaphylactic reactions, including anaphylactic shock

Psychiatric Disorders: Abnormal dreams and nightmares

8 USE IN SPECIFIC POPULATIONS

8.1 Pregnancy

Risk Summary

Limited available data with Mozobil use in pregnant women are insufficient to inform a drug-associated risk of adverse developmental outcomes. In animal reproduction studies, subcutaneous administration of plerixafor to pregnant rats during organogenesis at doses 10-times the maximum recommended human doses resulted in embryo-fetal mortality, structural abnormalities, and alterations to growth [see Data].

Advise pregnant women of the potential risk to the fetus.

Advise women of reproductive potential to avoid becoming pregnant while receiving treatment with Mozobil [see Warnings and Precautions (5.6)].

In the U.S. general population, the estimated background risk of major birth defects and miscarriage in clinically recognized pregnancies is 2% to 4% and 15% to 20%, respectively. All pregnancies have a background risk of birth defect, loss, or other adverse outcomes. The background risk of major birth defects and miscarriages for the indicated population is unknown.

Data

Animal data

Plerixafor administered to pregnant rats induced embryo-fetal toxicity, including fetal death, increased resorptions and postimplantation loss, decreased fetal weights, anophthalmia, shortened digits, cardiac interventricular septal defect, ringed aorta, globular heart, hydrocephaly, dilatation of olfactory ventricles, and retarded skeletal development. Embryo-fetal toxicities occurred mainly at a dose of 90 mg/m^2 (approximately 10 times the recommended human dose of 0.24 mg/kg when compared on a mg/m^2 basis).

8.2 Lactation

Risk Summary

There are no data on the presence of plerixafor in human milk, the effect on the breastfed child, or the effect on milk production. Because of the potential serious adverse reactions in the breastfed child, advise females that breastfeeding is not recommended during treatment with Mozobil and for one week after the final dose.

8.3 Females and Males of Reproductive Potential

Pregnancy Testing

Verify pregnancy status in females of reproductive potential prior to initiating Mozobil [see Use in Specific Populations (8.1)].

Contraception

Females

Mozobil can cause embryo-fetal harm when administered to pregnant women [see Use in Specific Populations (8.1)]. Advise females of reproductive potential to use effective contraception during treatment with Mozobil and for one week after the final dose.

Males

Males treated with Mozobil should use effective contraception during treatment and for one week after cessation of treatment.

8.4 Pediatric Use

The safety and effectiveness of Mozobil have not been established in pediatric patients. Effectiveness was not demonstrated in a single phase 1/2 randomized, open-label, comparative study of Mozobil plus standard regimens for mobilization of hematopoietic stem cells to the peripheral blood for collection and subsequent autologous transplantation. Forty-five pediatric patients ages 1 to <17 years with solid tumors or lymphoma were randomized 2:1 to Mozobil in addition to standard mobilization regimens (N=30) or standard mobilization regimens alone (N=15) (comparator arm). No new safety signals were observed in pediatric patients in this trial.

The day prior to the first apheresis, median peripheral blood CD34+ counts were 35 × 10^6 cells/L in the comparator arm and 15 × 10^6 cells/L in the Mozobil arm. On the day of the first apheresis, median peripheral blood CD34+ counts were 64 × 10^6 cells/L in the comparator arm and 77 × 10^6 cells/L in the Mozobil arm.

Plerixafor exposure, shown as AUC, in pediatric patients aged 12 to 18 years was within the range of values previously observed in adults, while the AUC of plerixafor in pediatric patients aged 2 to 12 years was 67% to 87% of that observed in adults, given the same adult dose (0.24 mg/kg).

8.5 Geriatric Use

Of the total number of subjects in controlled clinical studies of Mozobil, 24% were 65 and over, while 0.8% were 75 and over. No overall differences in safety or effectiveness were observed between these subjects and younger subjects, and other reported clinical experience has not identified differences in responses between the elderly and younger patients, but greater sensitivity of some older individuals cannot be ruled out.

Since plerixafor is mainly excreted by the kidney, no dose modifications are necessary in elderly individuals with normal renal function. In general, care should be taken in dose selection for elderly patients due to the greater frequency of decreased renal function with advanced age. Dosage adjustment in elderly patients with CLCR less than or equal to 50 mL/min is recommended [see Dosage and Administration (2.3) and Clinical Pharmacology (12.3)].

8.6 Renal Impairment

In patients with moderate and severe renal impairment (CLCR less than or equal to 50 mL/min), reduce the dose of Mozobil by one-third to 0.16 mg/kg [see Dosage and Administration (2.3) and Clinical Pharmacology (12.3)].

10 OVERDOSAGE

Based on limited data at doses above the recommended dose of 0.24 mg/kg SC, the frequency of gastrointestinal disorders, vasovagal reactions, orthostatic hypotension, and/or syncope may be higher.

11 DESCRIPTION

Mozobil (plerixafor) injection is a sterile, preservative-free, clear, colorless to pale-yellow, isotonic solution for subcutaneous injection. Each mL of the sterile solution contains 20 mg of plerixafor. Each single-dose vial is filled to deliver 1.2 mL of the sterile solution that contains 24 mg of plerixafor and 5.9 mg of sodium chloride in Water for Injection adjusted to a pH of 6.0 to 7.5 with hydrochloric acid and with sodium hydroxide, if required.

Plerixafor is a hematopoietic stem cell mobilizer with a chemical name 1,4-Bis((1,4,8,11-tetraazacyclotetradecan-1-yl)methyl)benzene. It has the molecular formula C28H54N8. The molecular weight of plerixafor is 502.79 g/mol. The structural formula is provided in Figure 1.

Figure 1: Structural Formula

Plerixafor is a white to off-white crystalline solid. It is hygroscopic. Plerixafor has a typical melting point of 131.5°C. The partition coefficient of plerixafor between 1-octanol and pH 7 aqueous buffer is <0.1.

12 CLINICAL PHARMACOLOGY

12.1 Mechanism of Action

Plerixafor is an inhibitor of the CXCR4 chemokine receptor and blocks binding of its cognate ligand, stromal cell-derived factor-1α (SDF-1α). SDF-1α and CXCR4 are recognized to play a role in the trafficking and homing of human hematopoietic stem cells (HSCs) to the marrow compartment. Once in the marrow, stem cell CXCR4 can act to help anchor these cells to the marrow matrix, either directly via SDF-1α or through the induction of other adhesion molecules. Treatment with plerixafor resulted in leukocytosis and elevations in circulating hematopoietic progenitor cells in mice, dogs and humans. CD34+ cells mobilized by plerixafor were capable of engraftment with long-term repopulating capacity up to one year in canine transplantation models.

12.2 Pharmacodynamics

Data on the fold increase in peripheral blood CD34+ cell count (cells/mcL) by apheresis day were evaluated in two placebo-controlled clinical studies in patients with NHL and MM (Study 1 and Study 2, respectively). The fold increase in CD34+ cell count (cells/mcL) over the 24-hour period starting from the day prior to the first apheresis and ending the next morning just before the first apheresis is summarized in Table 3. During this 24-hour period, a single dose of Mozobil or placebo was administered 10 to 11 hours prior to apheresis.

Table 3: Fold Increase in Peripheral Blood CD34+ Cell Count Following Pretreatment with Filgrastim and Administration of Plerixafor
Study | Mozobil and Filgrastim |  | Placebo and Filgrastim
Study | Median | Mean (SD) | Median | Mean (SD)
Study 1 | 5.0 | 6.1 (5.4) | 1.4 | 1.9 (1.5)
Study 2 | 4.8 | 6.4 (6.8) | 1.7 | 2.4 (7.3)

In pharmacodynamic studies of Mozobil in healthy volunteers, peak mobilization of CD34+ cells was observed between 6 and 9 hours after administration. In pharmacodynamic studies of Mozobil in conjunction with filgrastim in healthy volunteers, a sustained elevation in the peripheral blood CD34+ count was observed from 4 to 18 hours after plerixafor administration with a peak CD34+ count between 10 and 14 hours.

QT/QTc Prolongation

There is no indication of a QT/QTc prolonging effect of Mozobil in single doses up to 0.40 mg/kg. In a randomized, double-blind, crossover study, 48 healthy subjects were administered a single subcutaneous dose of plerixafor (0.24 mg/kg and 0.40 mg/kg) and placebo. Peak concentrations for 0.40 mg/kg Mozobil were approximately 1.8-fold higher than the peak concentrations following the 0.24 mg/kg single subcutaneous dose.

12.3 Pharmacokinetics

The single-dose pharmacokinetics of plerixafor 0.24 mg/kg were evaluated in patients with NHL and MM following pretreatment with filgrastim (10 mcg/kg once daily for 4 consecutive days). Plerixafor exhibits linear kinetics between the 0.04 mg/kg to 0.24 mg/kg dose range. The pharmacokinetics of plerixafor was similar across clinical studies in healthy subjects who received plerixafor alone and NHL and MM patients who received plerixafor in combination with filgrastim.

A population pharmacokinetic analysis incorporated plerixafor data from 63 subjects (NHL patients, MM patients, subjects with varying degrees of renal impairment, and healthy subjects) who received a single SC dose (0.04 mg/kg to 0.24 mg/kg) of plerixafor. A two-compartment disposition model with first order absorption and elimination was found to adequately describe the plerixafor concentration-time profile. Significant relationships between clearance and creatinine clearance (CLCR), as well as between central volume of distribution and body weight were observed. The distribution half-life (t1/2α) was estimated to be 0.3 hours and the terminal population half-life (t1/2β) was 5.3 hours in patients with normal renal function.

The population pharmacokinetic analysis showed that the mg/kg-based dosage results in an increased plerixafor exposure (AUC0–24h) with increasing body weight. In order to compare the pharmacokinetics and pharmacodynamics of plerixafor following 0.24 mg/kg-based and fixed (20 mg) doses, a follow-up trial was conducted in patients with NHL (N=61) who were treated with 0.24 mg/kg or 20 mg of plerixafor. The trial was conducted in patients weighing 70 kg or less. The fixed 20 mg dose showed 1.43-fold higher exposure (AUC0–10h) than the 0.24 mg/kg dose (Table 4). The fixed 20 mg dose also showed numerically higher response rate (5.2% [60.0% vs 54.8%] based on the local lab data and 11.7% [63.3% vs 51.6%] based on the central lab data) in attaining the target of ≥5 × 10^6 CD34+ cells/kg than the mg/kg-based dose. However, the median time to reach ≥5 × 10^6 CD34+ cells/kg was 3 days for both treatment groups, and the safety profile between the groups was similar. Based on these results, further analysis was conducted by FDA reviewers and a body weight of 83 kg was selected as an appropriate cut-off point to transition patients from fixed to weight based dosing.

Table 4: Systemic Exposure (AUC0–10h) Comparisons of Fixed and Weight-Based Regimens
Regimen | Geometric Mean AUC
Fixed 20 mg (n=30) | 3991.2
0.24 mg/kg (n=31) | 2792.7
Ratio (90% CI) | 1.43 (1.32,1.54)

There is limited experience with the 0.24 mg/kg dose of plerixafor in patients weighing above 160 kg. Therefore, the dose should not exceed that of a 160 kg patient (i.e., 40 mg/day if CLCR is greater than 50 mL/min and 27 mg/day if CLCR is less than or equal to 50 mL/min) [see Dosage and Administration (2.1, 2.3)].

Absorption

Peak plasma concentrations occurred at approximately 30 to 60 minutes after a SC dose.

Distribution

Plerixafor is bound to human plasma proteins up to 58%. The apparent volume of distribution of plerixafor in humans is 0.3 L/kg demonstrating that plerixafor is largely confined to, but not limited to, the extravascular fluid space.

Metabolism

The metabolism of plerixafor was evaluated with in vitro assays. Plerixafor is not metabolized as shown in assays using human liver microsomes or human primary hepatocytes and does not exhibit inhibitory activity in vitro towards the major drug metabolizing cytochrome P450 enzymes (1A2, 2A6, 2B6, 2C8, 2C9, 2C19, 2D6, 2E1 and 3A4/5). In in vitro studies with human hepatocytes, plerixafor does not induce CYP1A2, CYP2B6, or CYP3A4 enzymes. These findings suggest that plerixafor has a low potential for involvement in cytochrome P450-dependent drug-drug interactions.

Elimination

The major route of elimination of plerixafor is urinary. Following a 0.24 mg/kg dose in healthy volunteers with normal renal function, approximately 70% of the dose was excreted in the urine as the parent drug during the first 24 hours following administration. In studies with healthy subjects and patients, the terminal half-life in plasma ranges between 3 and 5 hours. At concentrations similar to what are seen clinically, plerixafor did not act as a substrate or inhibitor of P-glycoprotein in an in vitro study with MDCKII and MDCKII-MDR1 cell models.

Special Populations

Renal impairment

Following a single 0.24 mg/kg SC dose, plerixafor clearance was reduced in subjects with varying degrees of renal impairment and was positively correlated with CLCR. The mean AUC0–24h of plerixafor in subjects with mild (CLCR 51–80 mL/min), moderate (CLCR 31–50 mL/min), and severe (CLCR <31 mL/min) renal impairment was 7%, 32%, and 39% higher than healthy subjects with normal renal function, respectively. Renal impairment had no effect on Cmax. A population pharmacokinetic analysis indicated an increased exposure (AUC0–24h) in patients with moderate and severe renal impairment compared to patients with CLCR >50 mL/min. These results support a dose reduction of one-third in patients with moderate to severe renal impairment (CLCR ≤50 mL/min) in order to match the exposure in patients with normal renal function. The population pharmacokinetic analysis showed that the mg/kg-based dosage results in an increased plerixafor exposure (AUC0–24h) with increasing body weight; therefore, if CLCR is ≤50 mL/min the dose should not exceed 27 mg/day [see Dosage and Administration (2.3)].

Since plerixafor is primarily eliminated by the kidneys, coadministration of plerixafor with drugs that reduce renal function or compete for active tubular secretion may increase serum concentrations of plerixafor or the coadministered drug. The effects of coadministration of plerixafor with other drugs that are renally eliminated or are known to affect renal function have not been evaluated.

Race

Clinical data show similar plerixafor pharmacokinetics for Caucasians and African Americans, and the effect of other racial/ethnic groups has not been studied.

Gender

Clinical data show no effect of gender on plerixafor pharmacokinetics.

Age

Clinical data show no effect of age on plerixafor pharmacokinetics.

13 NONCLINICAL TOXICOLOGY

13.1 Carcinogenesis, Mutagenesis, Impairment of Fertility

Carcinogenicity studies with plerixafor have not been conducted.

Plerixafor was not genotoxic in an in vitro bacterial mutation assay (Ames test in Salmonella), an in vitro chromosomal aberration test using V79 Chinese hamster cells, or an in vivo bone marrow micronucleus test in rats after subcutaneous doses up to 25 mg/kg (150 mg/m^2).

The effect of plerixafor on human fertility is unknown. The effect of plerixafor on male fertility was not studied in designated reproductive toxicology studies. The staging of spermatogenesis measured in a 28-day repeated dose toxicity study in rats revealed no abnormalities considered to be related to plerixafor. No histopathological evidence of toxicity to male or female reproductive organs was observed in 28-day repeated dose toxicity studies.

No adverse effects on estrus or reproductive indices were observed in an investigative fertility study in female rats administered plerixafor at doses up to 90 mg/m^2 (15mg/kg/day) or approximately 10 times the recommended human dose of 0.24 mg/kg when compared on a mg/m^2 basis.

14 CLINICAL STUDIES

The efficacy and safety of Mozobil in conjunction with filgrastim in non-Hodgkin's lymphoma (NHL) Study AMD 3100-3101 (referred to as study 1) (NCT00103610) and multiple myeloma (MM) Study AMD 3100-3102 (referred to as study 2) (NCT00103662) were evaluated in two placebo-controlled studies (Studies 1 and 2). Patients were randomized to receive either Mozobil 0.24 mg/kg or placebo on each evening prior to apheresis. Patients received daily morning doses of filgrastim 10 mcg/kg for 4 days prior to the first dose of Mozobil or placebo and on each morning prior to apheresis. Two hundred and ninety-eight (298) NHL patients were included in the primary efficacy analyses for Study 1. The mean age was 55 years (range 29–75) and 58 years (range 22–75) in the Mozobil and placebo groups, respectively, and 93% of subjects were Caucasian. In study 2, 302 patients with MM were included in the primary efficacy analyses. The mean age (58 years) and age range (28–75) were similar in the Mozobil and placebo groups, and 81% of subjects were Caucasian.

In Study 1, 59% of NHL patients who were mobilized with Mozobil and filgrastim collected ≥5 × 10^6 CD34+ cells/kg from the peripheral blood in four or fewer apheresis sessions, compared with 20% of patients who were mobilized with placebo and filgrastim (p <0.001). Other CD34+ cell mobilization outcomes showed similar findings (Table 5).

Table 5: Study 1 Efficacy Results - CD34+ Cell Mobilization in NHL Patients
Efficacy Endpoint | Mozobil and Filgrastim (n=150) | Placebo and Filgrastim (n=148) | p-value [p-value calculated using Pearson's Chi-Squared test]
Patients achieving ≥5 × 10^6 cells/kg in ≤4 apheresis days | 89 (59%) | 29 (20%) | <0.001
Patients achieving ≥2 × 10^6 cells/kg in ≤4 apheresis days | 130 (87%) | 70 (47%) | <0.001

The median number of days to reach ≥5 × 10^6 CD34+ cells/kg was 3 days for the Mozobil group and not evaluable for the placebo group. Table 6 presents the proportion of patients who achieved ≥5 × 10^6 CD34+ cells/kg by apheresis day.

Table 6: Study 1 Efficacy Results – Proportion of Patients Who Achieved ≥5 × 10^6 CD34+ cells/kg by Apheresis Day in NHL Patients
Days | Proportion [Percents determined by Kaplan Meier method] in Mozobil and Filgrastim (n=147 [n includes all patients who received at least one day of apheresis]) | Proportion in Placebo and Filgrastim (n=142)
1 | 27.9% | 4.2%
2 | 49.1% | 14.2%
3 | 57.7% | 21.6%
4 | 65.6% | 24.2%

In Study 2, 72% of MM patients who were mobilized with Mozobil and filgrastim collected ≥6 × 10^6 CD34+ cells/kg from the peripheral blood in two or fewer apheresis sessions, compared with 34% of patients who were mobilized with placebo and filgrastim (p <0.001). Other CD34+ cell mobilization outcomes showed similar findings (Table 7).

Table 7: Study 2 Efficacy Results – CD34+ Cell Mobilization in Multiple Myeloma Patients
Efficacy Endpoint | Mozobil and Filgrastim (n=148) | Placebo and Filgrastim (n=154) | p-value [p-value calculated using Pearson's Chi-Squared test]
Patients achieving ≥6 × 10^6 cells/kg in ≤2 apheresis days | 106 (72%) | 53 (34%) | <0.001
Patients achieving ≥6 × 10^6 cells/kg in ≤4 apheresis days | 112 (76%) | 79 (51%) | <0.001
Patients achieving ≥2 × 10^6 cells/kg in ≤4 apheresis days | 141 (95%) | 136 (88%) | 0.028

The median number of days to reach ≥6 × 10^6 CD34+ cells/kg was 1 day for the Mozobil group and 4 days for the placebo group. Table 8 presents the proportion of patients who achieved ≥6 × 10^6 CD34+ cells/kg by apheresis day.

Table 8: Study 2 – Proportion of Patients Who Achieved ≥6 × 10^6 CD34+ cells/kg by Apheresis Day in MM Patients
Days | Proportion [Percents determined by Kaplan Meier method] in Mozobil and Filgrastim (n=144 [n includes all patients who received at least one day of apheresis]) | Proportion in Placebo and Filgrastim (n=150)
1 | 54.2% | 17.3%
2 | 77.9% | 35.3%
3 | 86.8% | 48.9%
4 | 86.8% | 55.9%

Multiple factors can influence time to engraftment and graft durability following stem cell transplantation. For transplanted patients in the Phase 3 studies, time to neutrophil and platelet engraftment and graft durability were similar across the treatment groups.

16 HOW SUPPLIED/STORAGE AND HANDLING

Mozobil® (plerixafor) injection 24 mg/1.2 mL (20 mg/mL) is a sterile, preservative-free, clear, colorless to pale-yellow solution supplied in a 2 mL clear glass single-dose vial.

NDC Number: 0024-5862-01

STORAGE AND HANDLING

Store at 25°C (77°F); excursions permitted to 15°C–30°C (59°F–86°F) [see USP Controlled Room Temperature].

17 PATIENT COUNSELING INFORMATION

Advise patients of the potential for anaphylactic reactions, including signs and symptoms such as urticaria, periorbital swelling, dyspnea, or hypoxia during and following Mozobil injection and to report these symptoms immediately to a healthcare professional [see Adverse Reactions (6.1, 6.2)].

Advise patients to contact healthcare professional immediately if they experience left upper abdominal pain and/or scapular or shoulder pain [see Adverse Reactions (6.1,6.2)].

Advise patients to inform a healthcare professional immediately if symptoms of vasovagal reactions such as orthostatic hypotension or syncope occur during or shortly after their Mozobil injection [see Adverse Reactions (6.1)].

Advise patients who experience itching, rash, or reaction at the site of injection to notify a healthcare professional, as these symptoms have been treated with over-the-counter medications during clinical trials [see Adverse Reactions (6.1)].

Advise patients that Mozobil may cause gastrointestinal disorders, including diarrhea, nausea, vomiting, flatulence, and abdominal pain. Patients should be told how to manage specific gastrointestinal disorders and to inform their healthcare professional if severe events occur following Mozobil injection [see Adverse Reactions (6.1)].

Advise females of reproductive potential of the potential risk to a fetus. Advise females to contact their healthcare provider if they become pregnant, or if pregnancy is suspected, during treatment with Mozobil [see Warnings and Precautions (5.6), Use in Specific Populations (8.1)].

Advise females and males of reproductive potential to use effective contraceptive methods during Mozobil use and for 1 week following cessation of treatment [see Warnings and Precautions (5.6), Use in Specific Populations (8.1)].

Advise women not to breastfeed during treatment with Mozobil and for 1 week following the last dose [Use in Specific Populations (8.2)].

Genzyme Corporation
Cambridge, MA 02141
A SANOFI COMPANY

©2023 Genzyme Corporation. All rights reserved.
Mozobil is a registered trademark of Genzyme Corporation.

PRINCIPAL DISPLAY PANEL - 24 mg/1.2 mL Vial Carton

NDC 0024-5862-01

Mozobil®
(plerixafor) injection

24 mg/1.2 mL
(20 mg/mL)

For subcutaneous
injection only

One single-dose vial.
Discard unused portion.

Rx only

SANOFI GENZYME